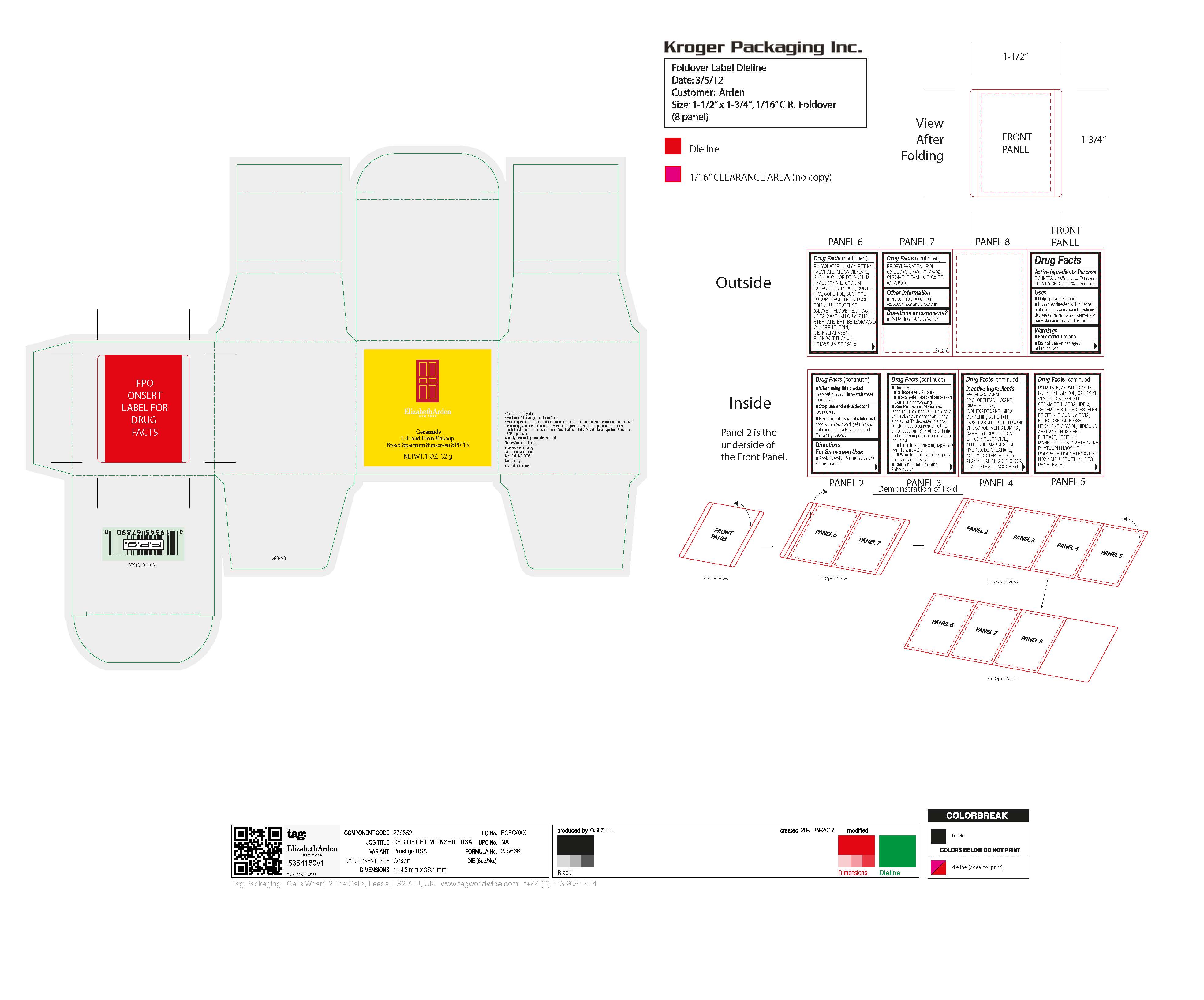 DRUG LABEL: CERAMIDE MAKEUP SPF 15
NDC: 10967-668 | Form: CREAM
Manufacturer: REVLON
Category: otc | Type: HUMAN OTC DRUG LABEL
Date: 20240112

ACTIVE INGREDIENTS: TITANIUM DIOXIDE 3 mg/1 g; OCTINOXATE 4 mg/1 g
INACTIVE INGREDIENTS: TOCOPHEROL; TREHALOSE; TRIFOLIUM PRATENSE FLOWER; BUTYLATED HYDROXYTOLUENE; BENZOIC ACID; METHYLPARABEN; POTASSIUM SORBATE; FERRIC OXIDE YELLOW; CAPRYLYL GLYCOL; EDETATE DISODIUM ANHYDROUS; FRUCTOSE; FERROSOFERRIC OXIDE; ALANINE; ALPINIA ZERUMBET LEAF; ABELMOSCHUS MOSCHATUS SEED; CHOLESTEROL; ANHYDROUS DEXTROSE; ACETYL OCTAPEPTIDE-3; MANNITOL; ASPARTIC ACID; BUTYLENE GLYCOL; CERAMIDE 1; PROPYLPARABEN; HEXYLENE GLYCOL; LECITHIN, SOYBEAN; SODIUM LAUROYL LACTYLATE; SUCROSE; WATER; ISOHEXADECANE; SORBITAN ISOSTEARATE; ASCORBYL PALMITATE; CARBOMER HOMOPOLYMER, UNSPECIFIED TYPE; CERAMIDE 3; CERAMIDE 6 II; PHENOXYETHANOL; UREA; XANTHAN GUM; CHLORPHENESIN; HYALURONATE SODIUM; CYCLOMETHICONE 5; GLYCERIN; MICA; ALUMINUM OXIDE; DIMETHICONE; DIMETHICONE CROSSPOLYMER (450000 MPA.S AT 12% IN CYCLOPENTASILOXANE); VITAMIN A PALMITATE; PHYTOSPHINGOSINE; POLYQUATERNIUM-51 (2-METHACRYLOYLOXYETHYL PHOSPHORYLCHOLINE/N-BUTYL METHACRYLATE; 3:7); SODIUM CHLORIDE; SORBITOL; FERRIC OXIDE RED

CERAMIDE LIFT AND FIRM MAKEUP BROAD SPECTRUM SUNSCREEN SPF 15

Active Ingredients Purpose

OCTINOXATE 4.0%.............. Sunscreen
TITANIUM DIOXIDE 3.0% .... Sunscreen

Inactive Ingredients

WATER/AQUA/EAU, CYCLOPENTASILOXANE, DIMETHICONE, ISOHEXADECANE, MICA, GLYCERIN, SORBITAN ISOSTEARATE, DIMETHICONE CROSSPOLYMER, ALUMINA, CAPRYLYL DIMETHICONE ETHOXY GLUCOSIDE, ALUMINUM/MAGNESIUM HYDROXIDE STEARATE, ACETYL OCTAPEPTIDE-3, ALANINE, ALPINIA SPECIOSA LEAF EXTRACT, ASCORBYL PALMITATE, ASPARTIC ACID, BUTYLENE GLYCOL, CAPRYLYL GLYCOL, CARBOMER, CERAMIDE 1, CERAMIDE 3, CERAMIDE 6 II, CHOLESTEROL, DEXTRIN, DISODIUM EDTA, FRUCTOSE, GLUCOSE, HEXYLENE GLYCOL, HIBISCUS ABELMOSCHUS SEED EXTRACT, LECITHIN, MANNITOL, PCA DIMETHICONE, PHYTOSPHINGOSINE, POLYPERFLUOROETHOXYMETHOXY DIFLUOROETHYL PEG PHOSPHATE, POLYQUATERNIUM-51, RETINYL PALMITATE, SILICA SILYLATE, SODIUM CHLORIDE, SODIUM HYALURONATE, SODIUM LAUROYL LACTYLATE, SODIUM PCA, SORBITOL, SUCROSE, TOCOPHEROL, TREHALOSE, TRIFOLIUM PRATENSE (CLOVER) FLOWER EXTRACT, UREA, XANTHAN GUM, ZINC STEARATE, BHT, BENZOIC ACID, CHLORPHENESIN, METHYLPARABEN, PHENOXYETHANOL, POTASSIUM SORBATE, PROPYLPARABEN, IRON OXIDES (CI 77491, CI 77492, CI 77499), TITANIUM DIOXIDE (CI 77891).

Uses

- Helps prevent sunburn
- If used as directed with other sun protection measures (see Directions), decreases the risk of skin cancer and early skin aging caused by the sun

Warnings

- For external use only
- Do not use on damaged or broken skin

- When using this product keep out of eyes. Rinse with water to remove.

- Stop use and ask a doctor if rash occurs.

- Keep out of reach of children. If product is swallowed, get medical help or contact a Poison Control Center right away.

Directions For Sunscreen Use

- Apply liberally 15 minutes before sun exposure
- Reapply:

- at least every 2 hours
- use a water resistant sunscreen if swimming or sweating
- Sun Protection Measures.
Spending time in the sun increases your risk of skin cancer and early skin aging. To decrease this risk, regularly use a sunscreen with a broad spectrum SPF of 15 or higher and other sun protection measures including:
- Limit time in the sun, especially from 10 a.m. – 2 p.m.
- Wear long-sleeve shirts, pants, hats, and sunglasses
- Children under 6 months: Ask a doctor.

DOSAGE AND ADMINISTRATION

As needed

INDICATIONS AND USAGE

Helps prevent sunburn

Keep out of reach of children. If swallowed seek medical help or contact a Poison Control Center right away.

PURPOSE

Sunscreen